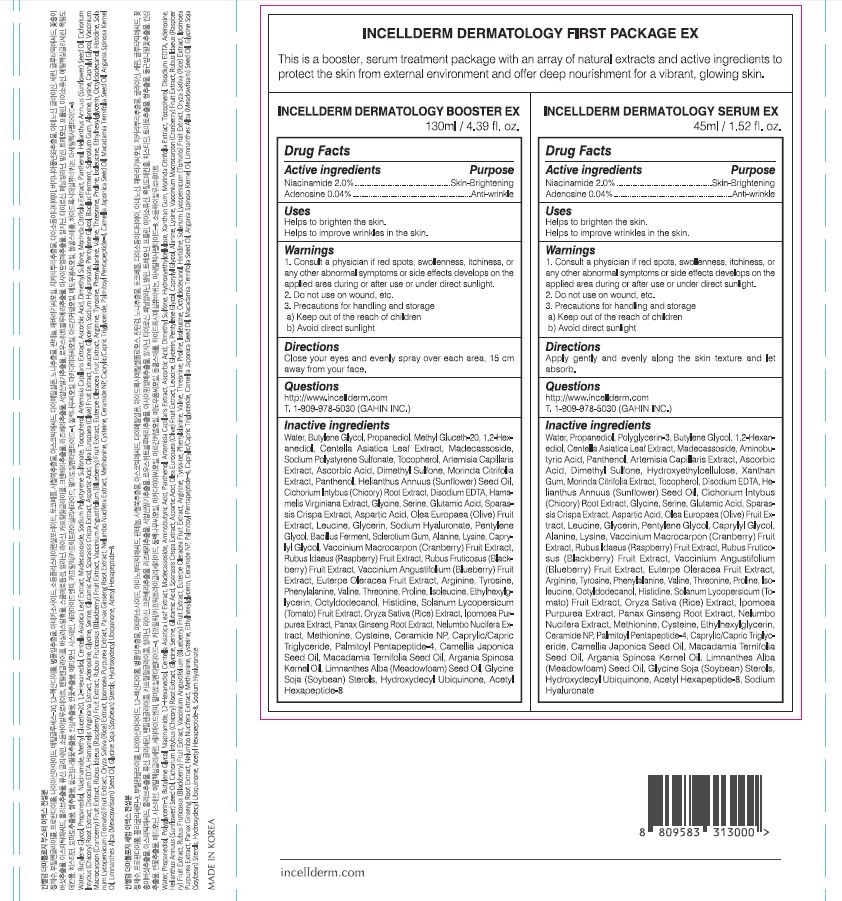 DRUG LABEL: INCELLDERM DERMATOLOGY SERUM EX
NDC: 72650-104 | Form: LIQUID
Manufacturer: Riman Korea Co., Ltd.
Category: otc | Type: HUMAN OTC DRUG LABEL
Date: 20210401

ACTIVE INGREDIENTS: NIACINAMIDE 2 g/100 mL; ADENOSINE 0.04 g/100 mL
INACTIVE INGREDIENTS: GLYCERIN; BUTYLENE GLYCOL

ACTIVE INGREDIENTS

Niacinamide, Adenosine

INACTIVE INGREDIENTS

Water, Propanediol, Polyglycerin-3, Butylene Glycol, 1,2-Hexanediol, Centella Asiatica Leaf Extract, Madecassoside, Aminobutyric Acid, Panthenol, Artemisia Capillaris Extract, Ascorbic Acid, Dimethyl Sulfone, Hydroxyethylcellulose, Xanthan Gum, MorindaCitrifolia Extract, Tocopherol, Disodium EDTA,Helianthus Annuus (Sunflower) Seed Oil, Cichorium Intybus (Chicory) Root Extract, Glycine, Serine, Glutamic Acid, SparassisCrispa Extract, Aspartic Acid, Olea Europaea (Olive) Fruit Extract, Leucine, Glycerin, Pentylene Glycol, Caprylyl Glycol, Alanine, Lysine, Vaccinium Macrocarpon (Cranberry) Fruit Extract, Rubus Idaeus (Raspberry) Fruit Extract, Rubus Fruticosus (Blackberry) Fruit Extract, Vaccinium Angustifolium (Blueberry) Fruit Extract, Euterpe Oleracea Fruit Extract, Arginine, Tyrosine, Phenylalanine, Valine, Threonine, Proline, Isoleucine, Octyldodecanol, Histidine, Solanum Lycopersicum (Tomato) Fruit Extract, Oryza Sativa (Rice) Extract, Ipomoea Purpurea Extract, Panax Ginseng Root Extract, Nelumbo Nucifera Extract, Methionine, Cysteine, Ethylhexylglycerin, Ceramide NP, Palmitoyl Pentapeptide-4, Caprylic/Capric Triglyceride, Camellia Japonica Seed Oil, Macadamia Ternifolia Seed Oil, Argania Spinosa Kernel Oil, Limnanthes Alba (Meadowfoam) Seed Oil, Glycine Soja (Soybean) Sterols, Hydroxydecyl Ubiquinone, Acetyl Hexapeptide-8, Sodium Hyaluronate

PURPOSE

Helps to brighten the skin.

Helps to improve wrinkles in the skin.

WARNINGS

1. Consult a physician if red spots, swollenness, itchiness, or any other abnormal symptoms or side effects develops on the applied area during or after use or under direct sunlight.

2. Do not use on wound, etc.

3. Precautions for handling and storage

a) Keep out of the reach of children

b) Avoid direct sunlight

KEEP OUT OF REACH OF CHILDREN

Uses

Apply gently and evenly along the skin texture and let absorb.

Directions

for external use only